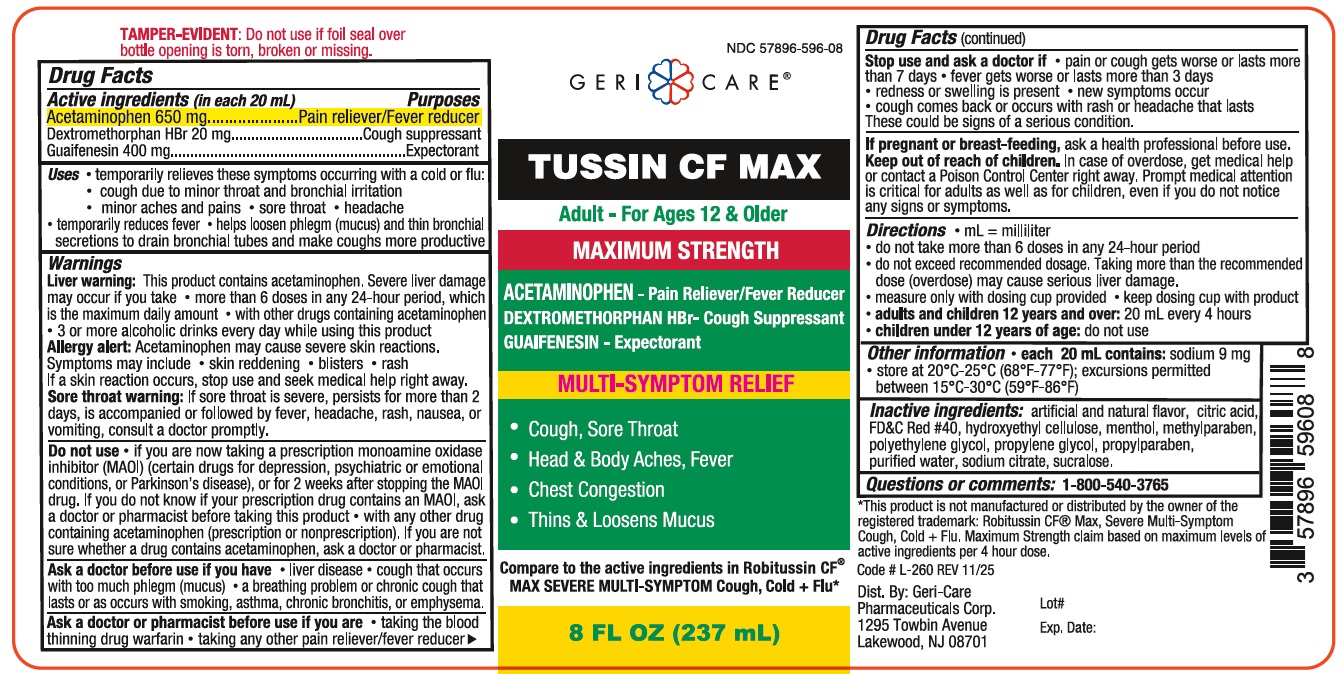 DRUG LABEL: Geri Care Tussin CF Max
NDC: 57896-596 | Form: LIQUID
Manufacturer: GERI-CARE PHARMACEUTICAL CORP
Category: otc | Type: HUMAN OTC DRUG LABEL
Date: 20251231

ACTIVE INGREDIENTS: ACETAMINOPHEN 650 mg/20 mL; DEXTROMETHORPHAN HYDROBROMIDE 20 mg/20 mL; GUAIFENESIN 400 mg/20 mL
INACTIVE INGREDIENTS: HYDROXYETHYL CELLULOSE, UNSPECIFIED; SUCRALOSE; ANHYDROUS CITRIC ACID; METHYLPARABEN; FD&C RED NO. 40; SODIUM CITRATE; POLYETHYLENE GLYCOL, UNSPECIFIED; PROPYLPARABEN; WATER; PROPYLENE GLYCOL; MENTHOL

GeriCare TussinCFMax 596

Active Ingredients (in each 20 mL)

Acetaminophen 650 mg

Dextromethorphan HBr 20 mg

Guaifenesin 400 mg

Purpose

Pain reliever/fever reducer

Cough Suppressant

Expectorant

Uses

- temporarily relieves these symptoms occurring with a cold or flu:
- cough due to minor throat and bronchial irritation
- minor aches and pains
- sore throat
- headache
- temporarily reduces fever
- helps loosen phlegm (mucus) and thin bronchial secretions to drain bronchial tunes and make coughs more productive

Warnings

Liver warning: This product contains acetaminophen. Severe liver damage may occur if you take

- more than 6 doses in any 24-hour period, which is the maximum daily amount
- with other drugs containing acetaminophen
- 3 or more alcoholic drinks every day while using this product

Allergy alert: Acetaminophen may cause severe skin reactions.

Symptoms may include

- skin reddening
- blisters
- rash

If skin reaction occurs, stop use and seek medical help right away

Sore throat warning: If sore throat is severe, persists for more than 2 days, is accompanied or followed by fever, headache, rash, nausea, or vomiting, consult a doctor promptly.

Do not use

- if you are now taking a prescription monoamine oxidase inhibitor (MAOI) (certain drugs for depression, psychiatric or emotional conditions, or Parkinson's disease), or for 2 weeks after stopping the MAOI drug. If you do not know if your prescription drug contains an MAOI, ask a doctor or pharmacist before taking this product
- with any other drug containing acetaminophen (prescription or nonprescritpion), if you are not sure whether a drug contains acetaminophen, ask a doctor or pharmacist.

Ask a doctor before use if you have

- liver disease
- cough that occurs with too much phlegm (mucus)
- a breathing problem or chronic cough that lasts or as occurs with smoking, asthma, chronic bronchitis, or emphysema

Ask a doctor or pharmacist before use if you are

- taking the blood thinning drug warfarin
- taking any other pain reliever/fever reducer

Stop use and ask a doctor if

- pain or cough gets worse or lasts more than 7 days
- fever gets worse or lasts more tha 3 days
- redness or swelling is present
- new symptoms occur
- cough comes back or occurs with rash or headhache that lasts

These could be sign of a serious condition.

PREGNANCY OR BREAST FEEDING

If pregnant or breast-feeding, ask a health professional before use.

Keep out of reach of children.

Directions

- mL = mililiter
- do not take more tha 6 doses in any 24-hour period
- do not exceed recommended dosage. Taking more than the recommeded dose (overdose) may cause serious liver damage
- measure only with dosing cup provided
- keep dosing cup with product
- adults and children 12 years and over: 20 mL every 4 hours
- children under 12 years of age: do not use

INACTIVE INGREDIENT

Inactive ingredients: artificial and natural flavor, citric acid, FD&C #40, hyroxyethyl cellulose, menthol, methylparaben, polyethylene glycol, propylene glycol, propylparaben, purified water, sodium citrate, sucralose

Questions or comments: 1-800-540-3765